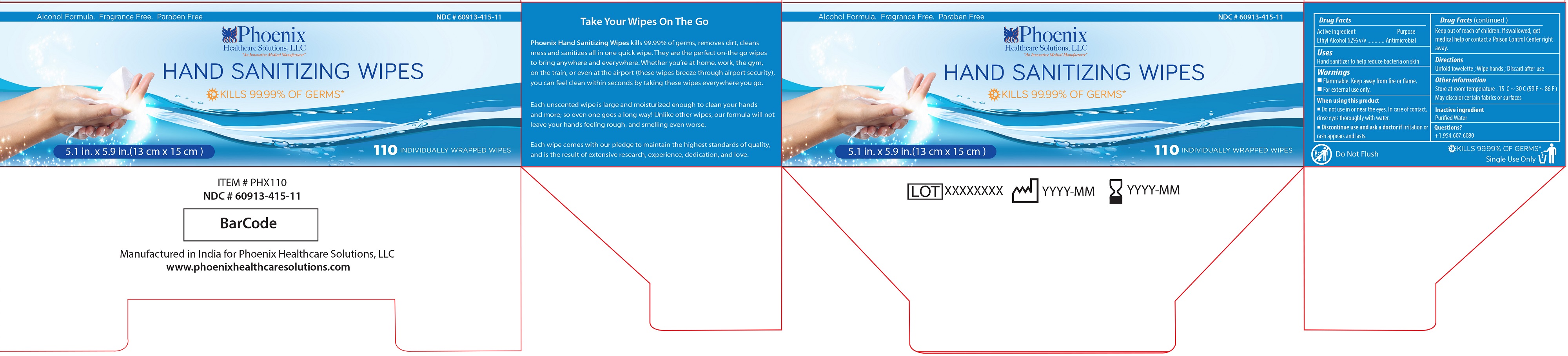 DRUG LABEL: Hand Sanitizing Wipes
NDC: 60913-415 | Form: CLOTH
Manufacturer: PHOENIX HEALTHCARE SOLUTIONS, LLC
Category: otc | Type: HUMAN OTC DRUG LABEL
Date: 20251023

ACTIVE INGREDIENTS: ALCOHOL 0.62 mL/1 mL
INACTIVE INGREDIENTS: WATER

Phoenix Hand Sanitizing Wipes

Active ingredient

Ethyl Alcohol 62% v/v

Purpose

Antimicrobial

Uses

Hand sanitizer to help reduce bacteria on the skin

Warnings

■ Flammable. Keep away from fire or flame.
■ For external use only.

When using this product

■ Do not use in or near the eyes. In case of contact, rinse eyes thoroughly with water.

Discontinue use and ask a doctor if

■ Irritation or rash appears and lasts.

Keep out of reach of Children

If swallowed, get medical help or contact a Poison Control Center right away.

Directions

Unfold towelette; Wipe hands; Discard after use

Inactive ingredient

Purified Water

Other information

■ Store at room temperature: 15℃~30℃(59℉~86℉)
■ May discolor certain fabrics or surfaces

Questions

+1-954-607-6080

Other Information

KILLS 99.99% OF GERMS*

Single Use Only

Do Not Flush

Principal Display Panel

NDC 60913-415-11

Alcohol Formula, Fragrance Free, Paraben Free

Phoenix Healthcare Solutions, LLC

"An Innovative Medical Manufacturer"

HAND SANITIZING WIPES

KILLS 99.99% OF GERMS*

5.1 in. X 5.9 in. (13 cm X 15 cm)

110 INDIVIDUALLY WRAPPED WIPES